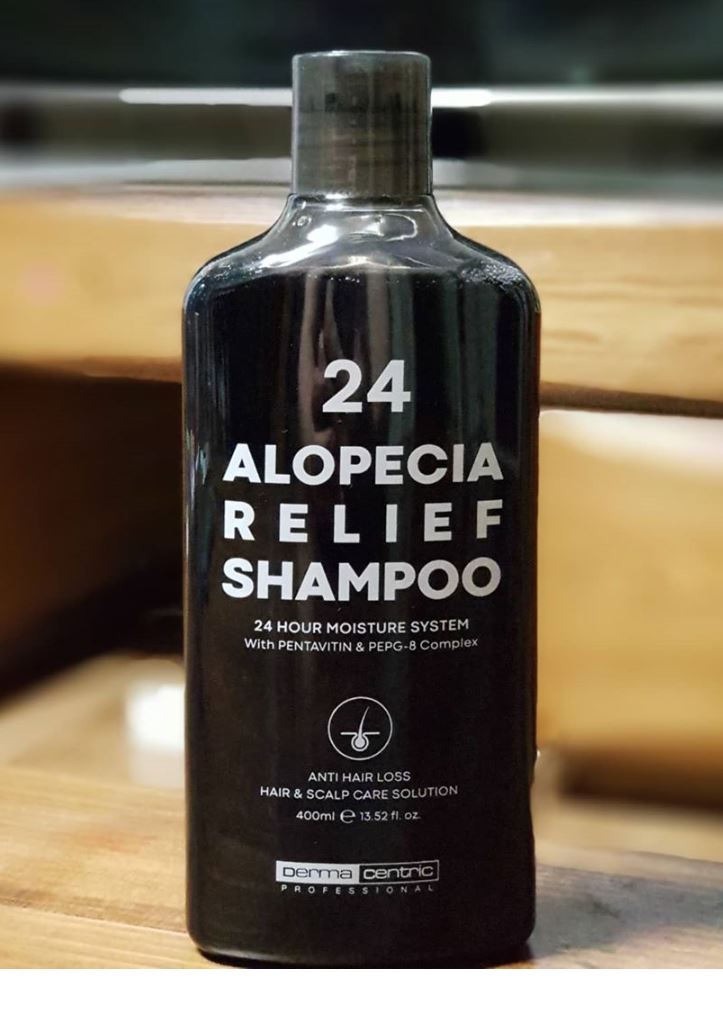 DRUG LABEL: 24 ALOPECIA RELIEFSHAMPOO
NDC: 79593-0004 | Form: SHAMPOO
Manufacturer: DERMA CENTRIC INC
Category: otc | Type: HUMAN OTC DRUG LABEL
Date: 20200808

ACTIVE INGREDIENTS: SALICYLIC ACID 0.25 g/100 mL; MENTHOL 0.3 g/100 mL; PANTHENOL 0.2 g/100 mL
INACTIVE INGREDIENTS: WATER; GLYCERIN

ACTIVE INGREDIENT

menthol, salicylic acid, panthenol

PURPOSE

hair care, ph balanced shampoo

KEEP OUT OF REACH OF THE CHILDREN

WARNINGS

■ For external use only.

■ Do not use in eyes.

■ lf swallowed, get medical help promptly.

■ Stop use, ask doctor lf irritation occurs.

■ Keep out of reach of children.

DOSAGE AND ADMINISTRATION

for external use only

INACTIVE INGREDIENT

WATER
COCAMIDOPROPYL BETAINE
SODIUM C14-16 OLEFIN SULFONATE
SODIUM METHYL COCOYL TAURATE
LAURYL BETAINE
SODIUM CHLORIDE
LAURYL HYDROXYSULTAINE
DECYL GLUCOSIDE
PPG-3 CAPRYLYL ETHER
CITRUS AURANTIUM DULCIS (ORANGE) OIL
PEAT WATER
GLYCINE SOJA (SOYBEAN) SEED EXTRACT
MORINDA CITRIFOLIA EXTRACT
MORUS ALBA ROOT EXTRACT
MAGNOLIA OFFICINALIS BARK EXTRACT
DIOSCOREA JAPONICA ROOT EXTRACT
CITRUS NOBILIS (MANDARIN ORANGE) PEEL OIL
EUTERPE OLERACEA FRUIT EXTRACT
AUREOBASIDIUM PULLULANS FERMENT
SALVIA HISPANICA SEED EXTRACT
CURCUMA LONGA (TURMERIC) ROOT EXTRACT
ARCTIUM LAPPA ROOT EXTRACT
LITSEA CUBEBA FRUIT OIL
LINUM USITATISSIMUM (LINSEED) SEED EXTRACT
ALOE BARBADENSIS LEAF EXTRACT
ORIGANUM VULGARE LEAF EXTRACT
HIBISCUS ESCULENTUS FRUIT EXTRACT
CHAMAECYPARIS OBTUSA LEAF EXTRACT
SALIX ALBA (WILLOW) BARK EXTRACT
LACTOBACILLUS/SOYBEAN FERMENT EXTRACT
PORTULACA OLERACEA EXTRACT
CINNAMOMUM CASSIA BARK EXTRACT
SCUTELLARIA BAICALENSIS ROOT EXTRACT
SARGASSUM FULVELLUM EXTRACT
GELIDIUM CARTILAGINEUM EXTRACT
HIZIKIA FUSIFORME EXTRACT
MILK PROTEIN EXTRACT
DIOSPYROS KAKI FRUIT EXTRACT
CAMELLIA JAPONICA LEAF EXTRACT
CERATONIA SILIQUA (CAROB) FRUIT EXTRACT
PANAX GINSENG ROOT EXTRACT
EMPETRUM NIGRUM FRUIT JUICE
THEOBROMA CACAO (COCOA) EXTRACT
MORINGA OLEIFERA SEED EXTRACT
LEUCONOSTOC/RADISH ROOT FERMENT FILTRATE
ORYZA SATIVA (RICE) BRAN OIL
PAULLINIA CUPANA SEED EXTRACT
SALVIA MILTIORRHIZA ROOT EXTRACT
PTYCHOPETALUM OLACOIDES BARK EXTRACT
COCAMIDE MEA
SACCHARIDE ISOMERATE
CITRIC ACID
SODIUM BENZOATE
POLYQUATERNIUM-47
DISODIUM EDTA
ACACIA SENEGAL GUM
BUTYLENE GLYCOL
SACCHARIDE HYDROLYSATE
HYDROXYPROPYL METHYLCELLULOSE
GLYCINE
1,2-HEXANEDIOL
SERINE
GLUTAMIC ACID
ASPARTIC ACID
GLYCERIN
LEUCINE
ALANINE
LYSINE
HYDROLYZED CORN PROTEIN
ARGININE
TYROSINE
PHENYLALANINE
VALINE
THREONINE
PROLINE
HYDROLYZED WHEAT PROTEIN
HYDROLYZED SOY PROTEIN
ISOLEUCINE
HISTIDINE
METHIONINE
CYSTEINE
HYDROLYZED KERATIN
HYDROLYZED RICE PROTEIN
CAPRYLYL GLYCOL
MADECASSOSIDE
ECTOIN
HYDROLYZED LUPINE PROTEIN
ETHYL HEXANEDIOL
GLYCINE SOJA (SOYBEAN) PROTEIN
MALTODEXTRIN
SUPEROXIDE DISMUTASE
HYDROLYZED COLLAGEN
CAFFEINE
NONAPEPTIDE-1
SODIUM DEXTRAN SULFATE
ACETYL HEXAPEPTIDE-8
COPPER TRIPEPTIDE-1
TRIPEPTIDE-1
PALMITOYL TETRAPEPTIDE-7
PALMITOYL TRIPEPTIDE-1
PALMITOYL PENTAPEPTIDE-4
HEXAPEPTIDE-9
CERAMIDE NP
PHYTOSPHINGOSINE
HYDROGENATED LECITHIN

INDICATIONS AND USAGE

combine hair before shampoo to remove large dust

gently massage shampoo into wet hair and scalp all over your tips

rinse to remove any remaining dubbles

tap wet hair with a toweland let it dry in natural or cold wind